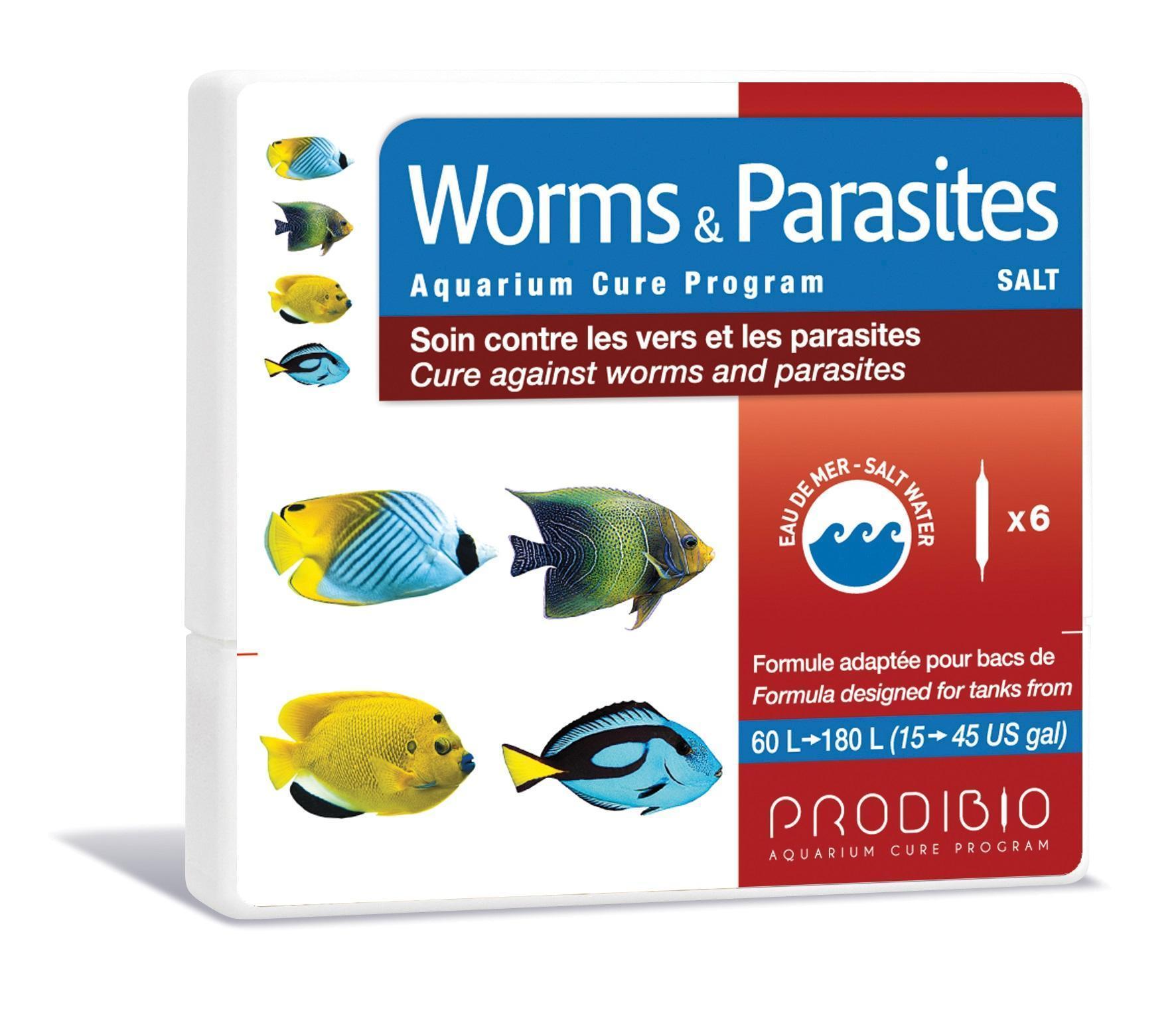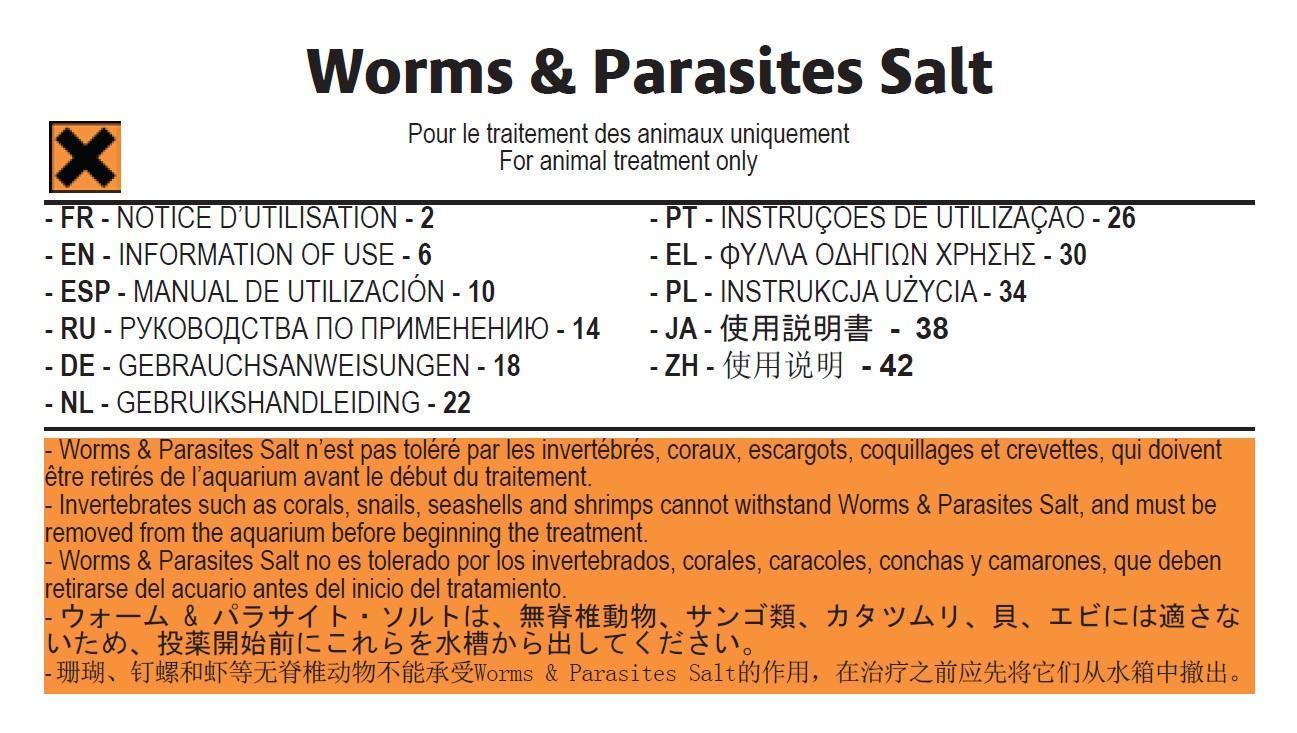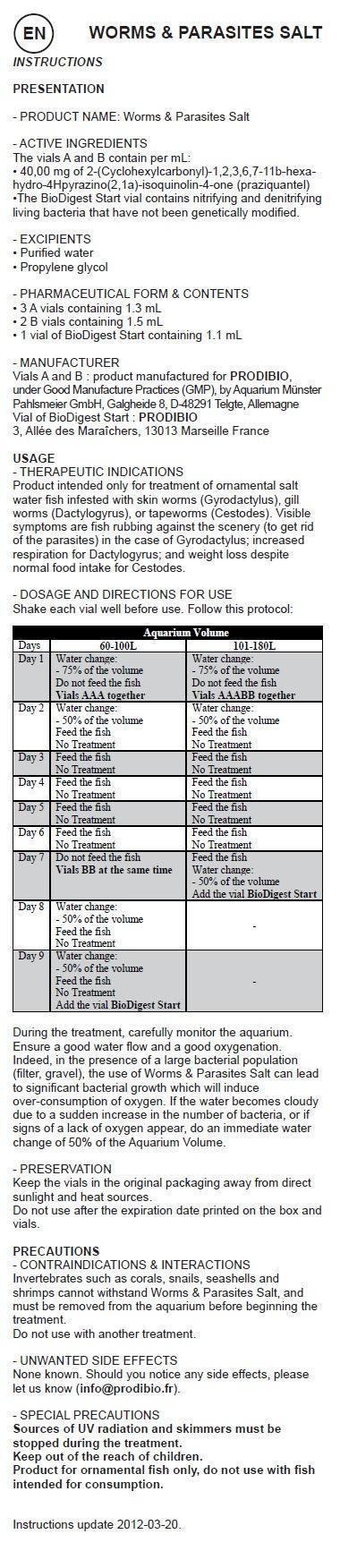 DRUG LABEL: Worm and Parasites Aquarium Cure Program Salt
NDC: 86048-003 | Form: KIT | Route: ORAL
Manufacturer: Prodibio SAS
Category: animal | Type: OTC ANIMAL DRUG LABEL
Date: 20150828

ACTIVE INGREDIENTS: PRAZIQUANTEL 40 mg/1 mL; PRAZIQUANTEL 40 mg/1 mL
INACTIVE INGREDIENTS: WATER; PROPYLENE GLYCOL; WATER; PROPYLENE GLYCOL

Worm & Parasites Aquarium Cure Program Salt

- PRODUCT NAME: Worms & Parasites Salt

- ACTIVE INGREDIENTS

The vials A and B contain per mL:
• 40,00 mg of 2-(Cyclohexylcarbonyl)-1,2,3,6,7-11b-hexahydro-4Hpyrazino(2,1a)-isoquinolin-4-one (praziquantel)
•The BioDigest Start vial contains nitrifying and denitrifying living bacteria that have not been genetically modified.

- EXCIPIENTS

• Purified water
• Propylene glycol

- PHARMACEUTICAL FORM & CONTENTS

• 3 A vials containing 1.3 mL
• 2 B vials containing 1.5 mL
• 1 vial of BioDigest Start containing 1.1 mL

- MANUFACTURER

Vials A and B : product manufactured for PRODIBIO, under Good Manufacture Practices (GMP), by Aquarium Münster Pahlsmeier GmbH, Galgheide 8, D-48291 Telgte, Allemagne

Vial of BioDigest Start : PRODIBIO 3, Allée des Maraîchers, 13013 Marseille France

USAGE

- THERAPEUTIC INDICATIONS
Product intended only for treatment of ornamental freshwater fish infested with skin worms (Gyrodactylus), gill worms (Dactylogyrus), or tapeworms (Cestodes). Visible symptoms are fish rubbing against the scenery (to get rid of the parasites) in the case of Gyrodactylus; increased respiration for Dactylogyrus; and weight loss despite normal food intake for Cestodes.

- DOSAGE AND DIRECTIONS FOR USE

Shake each vial well before use. Follow this protocol:

Aquarium Volume
Days | 60-100L | 101-180L
Day 1 | Water change: - 75% of the volume Do not feed the fish Vials AAA together | Water change: - 75% of the volume Do not feed the fish Vials AAABB together
Day 2 | Water change: - 50% of the volume Feed the fish No Treatment | Water change: - 50% of the volume Feed the fish No Treatment
Day 3 | Feed the fish No Treatment | Feed the fish No Treatment
Day 4 | Feed the fish No Treatment | Feed the fish No Treatment
Day 5 | Feed the fish No Treatment | Feed the fish No Treatment
Day 6 | Feed the fish No Treatment | Feed the fish No Treatment
Day 7 | Do not feed the fish Vials BB at the same time | Feed the fish Water change: - 50% of the volume Add the vial BioDigest Start
Day 8 | Water change: - 50% of the volume Feed the fish No Treatment
Day 9 | Water change: - 50% of the volume Feed the fish No Treatment Add the vial BioDigest Start

During the treatment, carefully monitor the aquarium. Ensure a good water flow and a good oxygenation. Indeed, in the presence of a large bacterial population (filter, gravel), the use of Worms & Parasites Fresh can lead to significant bacterial growth which will induce over-consumption of oxygen. If the water becomes cloudy due to a sudden increase in the number of bacteria, or if signs of a lack of oxygen appear, do an immediate water change of 50% of the Aquarium Volume.

- PRESERVATION

Keep the vials in the original packaging away from direct sunlight and heat sources.
Do not use after the expiration date printed on the box and vials.

PRECAUTIONS - CONTRAINDICATIONS & INTERACTIONS

Invertebrates such as snails and shrimps cannot withstand Worms & Parasites Fresh, and must be removed from the aquarium before beginning the treatment.
Do not use with another treatment.

- UNWANTED SIDE EFFECTS

None known. Should you notice any side effects, please let us know (info@prodibio.fr).

- SPECIAL PRECAUTIONS

Sources of UV radiation and skimmers must be stopped during the treatment.
Product for ornamental fish only, do not use with fish intended for consumption.